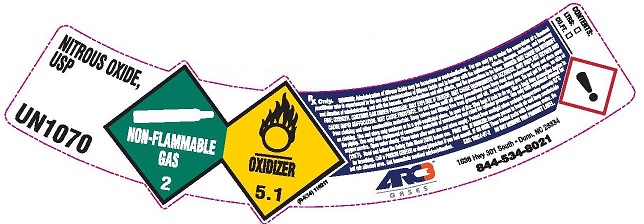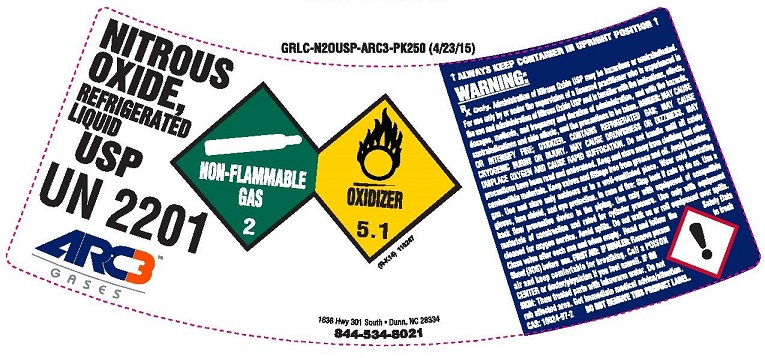 DRUG LABEL: Nitrous Oxide
NDC: 49575-013 | Form: GAS
Manufacturer: Machine & Welding Supply Company dba Arc3 Gases South
Category: animal | Type: PRESCRIPTION ANIMAL DRUG LABEL
Date: 20251202

ACTIVE INGREDIENTS: Nitrous Oxide 990 mL/1 L

Nitrous Oxide Label

PACKAGE LABEL

NITROUS OXIDE USP UN1070 NON-FLAMMABLE GAS 2 OXIDIZER 5.1
Rx only. WARNING: Administration of Nitrous Oxide may be hazardous or contraindicated. For use only by or under the supervision of a licensed practitioner who is experienced in the use and administration of Nitrous Oxide and is familiar with the indications, effects, dosages, methods, and frequency and duration of administration, and with the hazards, contraindications and side effects, and the precautions to be taken. DANGER: MAY CAUSE OR INTENSIFY FIRE; OXIDIZER CONTAINS GAS UNDER PESSURE; MAY EXPLODE IF HEATED. MAY CUASE DROWSINESS OR DIZZINESS. MAY DISPLACE OXYGEN AND CAUSE RAPID SUFFOCATION. MAY CAUSE FROSTBITE. Do not handle until all safety precautions have been read and understood. Keep and store away from clothing and other combustible materials. Keep valves and fittings free from grease and oil. Avoid breathing gas. Do not put in eyes on skin or on clothing. Use and store only outdoors or in a well-ventilated place. In case of fire: stop leak if safe to do so. Use a back flow preventive device in the piping. Use only with equipment of compatible materials of construction and rated for cylinder pressure. Use only with equipment cleaned for oxygen service. Open valve slowly. Close valve after each use and when empty. Protect from sunlight when ambient temperature exceeds 52 degrees C (125 degrees F). Read and follow the Safety Data Sheet (SDS) before use. FIRST AID: IF INHALED: Remove person to fresh air and keep comfortable for breathing. Call a POISON CENTER or doctor/physician if you feel unwell. IF ON SKIN: Thaw frosted parts with lukewarm water. Do not rub affected area. Get immediate medical advice/attention. CAS: 10024-97-2 DO NOT REMOVE THIS LABEL.
ARC3 GASES 1636 Hwy 301 South Dunn, NC 28334 844-534-8021

PACKAGE LABEL

NITROUS OXIDE, REFRIGERATED LIQUID USP UN2201 ARC3 GASES NON-FLAMMABLE GAS 2 OXIDIZER 5.1 1636 Hwy 301 South . Dunn, NC 28334 844-534-8021
ALWAYS KEEP CONTAINER IN UPRIGHT POSITION
NET CONTENTS Part # LBS C.F. Liters LQ NO-USP-L1 404 3519 99,654
WARNING: RX Only Administration of Nitrous Oxide may be hazardous or contraindicated. For use only by or under the supervision of a licensed practitioner who is experienced in the use and administration of Nitrous Oxide and is familiar with the indications, effects, dosages, methods, and frequency and duration of administration, and with the hazards, contraindications and side effects, and the precautions to be taken. DANGER: MAY CAUSE OR INTENSIFY FIRE; OXIDIZER CONTAINS GAS UNDER PESSURE; MAY EXPLODE IF HEATED. MAY CUASE DROWSINESS OR DIZZINESS. MAY DISPLACE OXYGEN AND CAUSE RAPID SUFFOCATION. MAY CAUSE FROSTBITE. Do not handle until all safety precautions have been read and understood. Keep and store away from clothing and other combustible materials. Keep valves and fittings free from grease and oil. Avoid breathing gas. Do not put in eyes on skin or on clothing. Use and store only outdoors or in a well-ventilated place. In case of fire: stop leak if safe to do so. Use a back flow preventive device in the piping. Use only with equipment of compatible materials of construction and rated for cylinder pressure. Use only with equipment cleaned for oxygen service. Open valve slowly. Close valve after each use and when empty. Protect from sunlight when ambient temperature exceeds 52 degrees C (125 degrees F). Read and follow the Safety Data Sheet (SDS) before use. FIRST AID: IF INHALED: Remove person to fresh air and keep comfortable for breathing. Call a POISON CENTER or doctor/physician if you feel unwell. IF ON SKIN: Thaw frosted parts with lukewarm water. Do not rub affected area. Get immediate medical advice/attention CAS: 10024-97-2 DO NOT REMOVE THIS LABEL